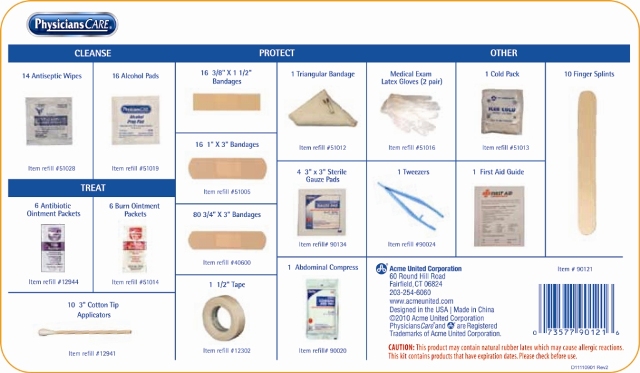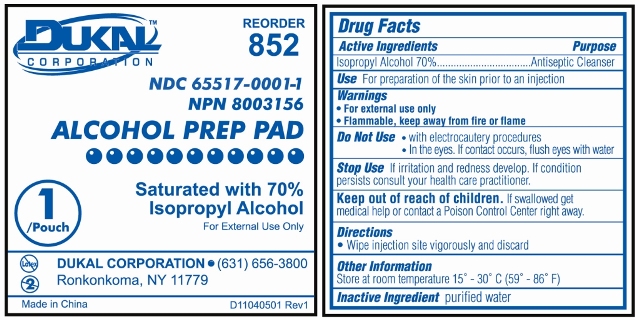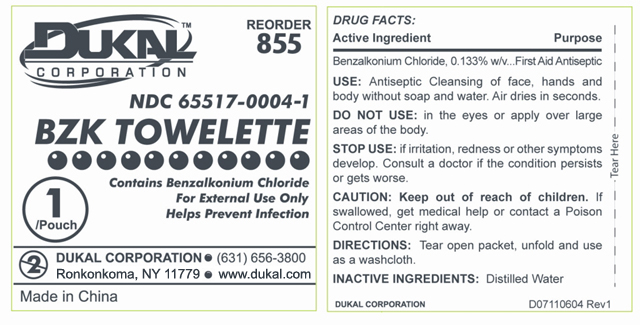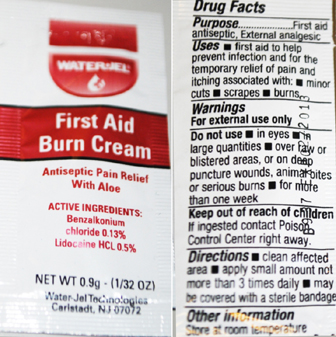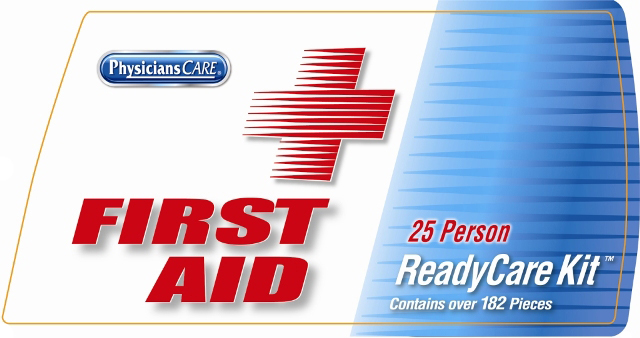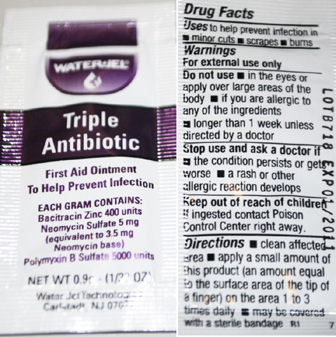 DRUG LABEL: Ready Care Kit
NDC: 65517-0020 | Form: KIT | Route: TOPICAL
Manufacturer: Dukal Corporation
Category: other | Type: MEDICAL DEVICE
Date: 20100923

ACTIVE INGREDIENTS: ISOPROPYL ALCOHOL 0.70 mL/1.0 mL; BACITRACIN ZINC 400 [iU]/1 g; NEOMYCIN SULFATE 3.5 mg/1 g; POLYMYXIN B SULFATE 5000 [iU]/1 g; BENZALKONIUM CHLORIDE 0.13 g/100 g; LIDOCAINE HYDROCHLORIDE 0.5 g/100 g; BENZALKONIUM CHLORIDE 0.00186 mL/1.4 mL
INACTIVE INGREDIENTS: PETROLATUM; EDETATE DISODIUM; LIGHT MINERAL OIL; STEARIC ACID; POLYETHYLENE GLYCOL; CETYL ALCOHOL; TROLAMINE; GLYCERIN; METHYLPARABEN; PROPYLENE GLYCOL; DIAZOLIDINYL UREA; ALOE VERA LEAF; WATER; PROPYLPARABEN; GLYCERYL MONOSTEARATE; WATER 1.39814 mL/1.4 mL

Front Label

PACKAGE LABEL

Physicians Care

FIRST AID

25 Person

ReadyCare Kit

Contains over 182 Pieces

Back Label

Physicians Care

CLEANSE

Antiseptics

14 Antiseptic Wipes
16 Alcohol Pads

TREAT

6 Antibiotic Ointment Packets
6 Burn Ointment Packets
10 3" Cotton Tip Applicator

PROTECT

16 3/8” x 1 1/2” Bandages
16 1” x 3” Bandages
80 3/4” x 3” Bandages
1 1/2" Tape
1 Triangular Bandage
4 3" x 3" Sterile Gauze Pads
1 Abdominal Compress

Other

Medical Exam Latex Gloves (2 Pair)
1 Tweezers
1 Cold Pack
1 First Aid Guide
10 Finger Splints

Acme United Corporation
60 Round Hill Road
Fairfield CT 06824
www.acmeunited.com
Designed in the USA | Made in China
CAUTION: This product may contain natural rubber latex which may cause allergic reactions.
This kit contains products that have expiration dates. Please check before use.

BZK Towelette Labeling

Reorder 855

NDC 65517-0004-1

Dukal

BZK TOWELETTE

Contains Benzalkonium Chloride

For External Use Only

Helps Prevent Infection

1 / Pouch

DUKAL CORPORATION

(631) 656-3800

Ronkonkoma, NY 11779 www.dukal.com

Made in China

Drug Facts

Active Ingredients..................... Benzalkonium Chloride 0.133% w/v

Purpose................................. First Aid Antiseptic

USE: Antiseptic Cleansing of face, hands and
body without soap and water. Airs dries in seconds

DO NOT USE: in the eyes or apply over large
areas of the body.

STOP USE: If irritation, redness or other symptoms
develop. Consult a doctor if the conditions persists
or gets worse.

CAUTION: Keep out of reach of children. If
swallowed get medical help or contact a Poison
Control Center right away.

DIRECTIONS: Tear open packet, unfold and use
as a washcloth.

INACTIVE INGREDIENTS: Distilled Water

Prep Pad Labeling

Reorder 852

Dukal Corporation

NDC 65517-0001-1

NPN 80003156

ALCOHOL PREP PAD

Saturated with 70% Isopropyl Alcohol

For External Use Only

1 / Pouch

Dukal Corporation

Ronkonkoma, NY 11779

631-656-3800

www.dukal.com

Made in China

Drug Facts

Active Ingredients

Isopropyl Alcohol 70%

Purpose

Antiseptic Cleanser

Use

For Preparation of Skin prior to an injection

Warnings

- For External Use Only
- Flammable, Keep away from fire or flame

Do Not Use

- with electrocautery procedures
- In the Eyes. If contact occurs, flush eyes with water

Stop Use

If irritation and redness develop. If condition persists, consult your health care practitioner.

Keep out of reach of children

If swallowed, get medical help or contact a Poison Control Center right away.

Directions

Wipe injection site vigorously and discard.

Other Information

Store at Room Temperature 15 - 30 C (59 - 86 F)

Inactive Ingredient

purified water

Triple Antibiotic Labeling

WaterJel

Triple Antibiotic

First Aid Ointment

To Help Prevent Infection

Each Gram contains

Bacitracin Zinc 400 units

Neomycin Sulphate 5 mg

(equivalent to 3.5 mg Neomycin base)

Polymyxin B Sulfate 5000 units

Water-Jel Technologies

Carlstadt, NJ 07072

Drug Facts

Uses to help prevent infection in

minor cuts, scrapes, burns

Warnings

For external use only

Do not use

in the eyes or apply over large areas of the body

If you are allergic to any of the ingredients

longer than 1 week unless directed by a doctor

Stop use and ask a doctor if

the condition persists or gets worse

a rash or other allergic reaction develops

Keep out of reach of children

if ingested contact Poison Control Center right away

Directions

clean affected area apply a small amount of product

(an amount equal to the surface area of the tip of a finger)

on the area 1 to 3 times daily may be covered with a sterile bandage

First Aid Burn Cream Labeling

WaterJel

First Aid Burn Cream

Antiseptic Pain Relief with Aloe

Active Ingredients:

Benzalkonium Chloride 0.13%

Lidocaine HCL 0.5%

Water-Jel Technologies

Carlstadt, NJ 07072

Drug Facts

Purpose

First Aid Antiseptic, External analgesic

Uses

first aid to help prevent infection and for temporary

relief of pain an itching associated with minor cuts,

scrapes, burns

Warnings

For external use only

Do not use

in the eyes

in large quantities over raw or blistered areas or on

deep puncture wounds, animal bites, or serious burns

Keep out of reach of children

if ingested contact Poison Control Center right away

Directions

clean affected area apply a small amount not more

than 3 times daily may be covered with a sterile bandage

Other Information

Store at room temperature